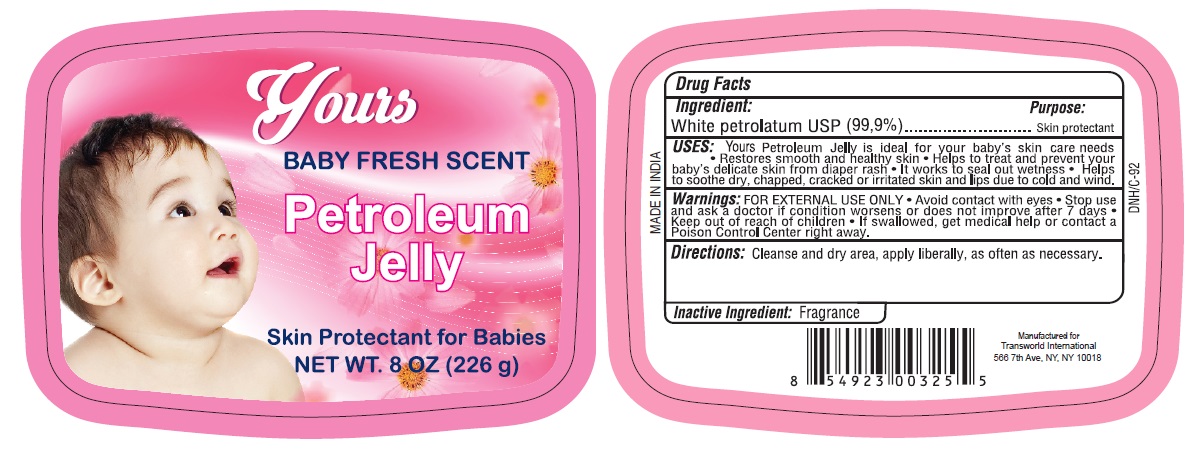 DRUG LABEL: Yours Baby Fresh Scent Petroleum
NDC: 71265-002 | Form: JELLY
Manufacturer: TRANSWORLD INTERNATIONAL TRADING CORP.
Category: otc | Type: HUMAN OTC DRUG LABEL
Date: 20170302

ACTIVE INGREDIENTS: PETROLATUM 99.9 g/100 g

Yours Baby Fresh Scent Petroleum Jelly

Active Ingredient

White Petrolatum USP (99.9%)

Purpose

Skin Protectant

Uses

- Yous Petroleum Jelly is ideal for your baby's skin care needs.
- Restores smooth and healthy skin.
- Helps to treat and prevent your baby's delicate skin from diaper rash.
- It works to seal out wetness.
- Helps to soothe dry, chapped, cracked or irritated skin and lips due to cold and wind.

Warnings

For External Use Only.

When using this product

- Avoid contact with eyes.

Stop use and ask a doctor

- If condition worsens or does not improve after 7 days.

Keep out of reach of children

- If swallowed get medical help or contact a Poison Control Center right away.

Directions

Cleanse and dry area, apply liberally, as often as necessary.

Inactive Ingredient

Fragrance

PACKAGE LABEL

PRINCIPAL DISPLAY PANEL

YOURS BABY FRESH SCENT PETROLEUM JELLY

NET WT. 8OZ. (226 g)